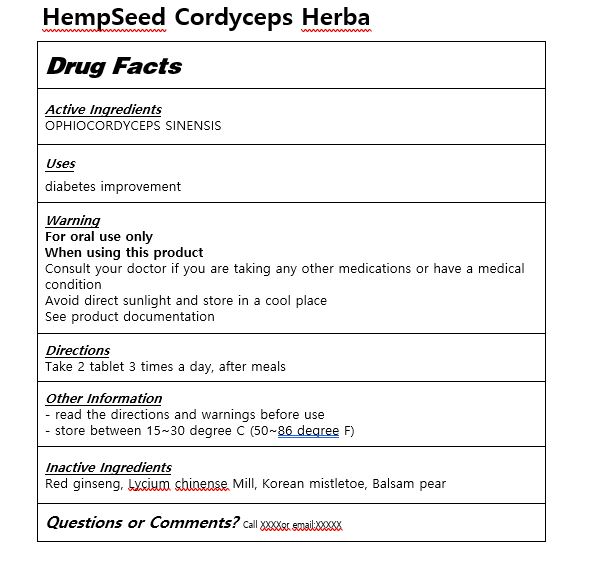 DRUG LABEL: HempSeed Cordyceps Herba
NDC: 83036-0002 | Form: CAPSULE
Manufacturer: Tong Cheon Dang
Category: otc | Type: HUMAN OTC DRUG LABEL
Date: 20221010

ACTIVE INGREDIENTS: OPHIOCORDYCEPS SINENSIS 0.1 g/1 1
INACTIVE INGREDIENTS: ASIAN GINSENG

ACTIVE INGREDIENT

OPHIOCORDYCEPS SINENSIS

INACTIVE INGREDIENT

Red ginseng, Lycium chinense Mill, Korean mistletoe, Balsam pear

PURPOSE

diabetes improvement

keep out of reach of the children

INDICATIONS AND USAGE

Take 2 tablet 3 times a day, after meals

WARNINGS

Consult your doctor if you are taking any other medications or have a medical condition
Avoid direct sunlight and store in a cool place
See product documentation

DOSAGE AND ADMINISTRATION

for oral use only